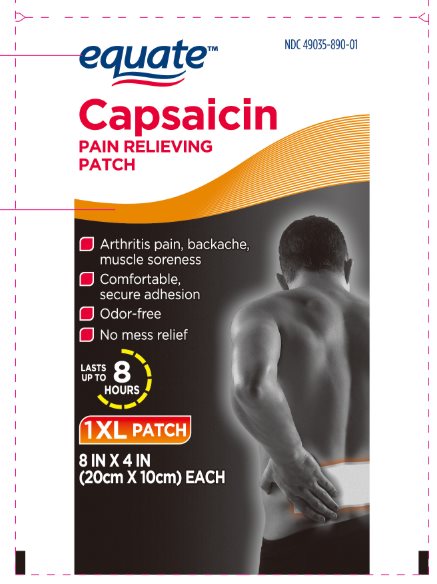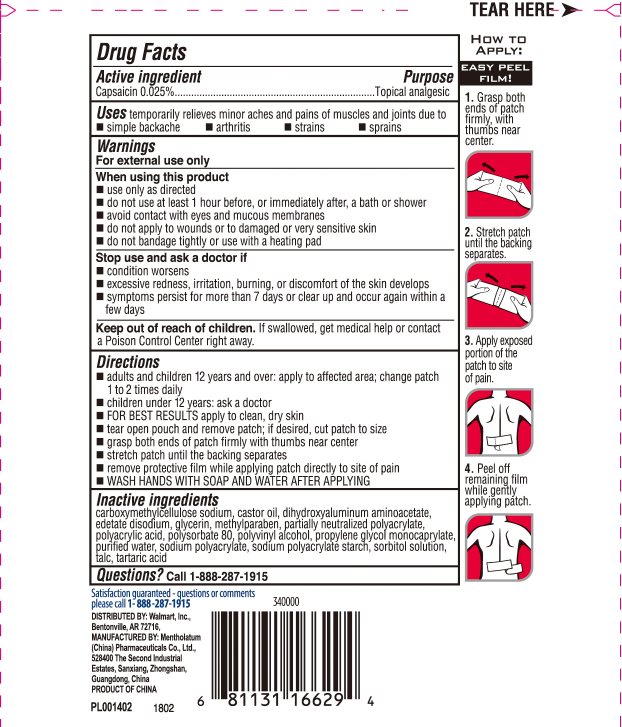 DRUG LABEL: Equate Capsaicin Pain Relieving
NDC: 49035-890 | Form: PATCH
Manufacturer: Wal-Mart Stores Inc
Category: otc | Type: HUMAN OTC DRUG LABEL
Date: 20241217

ACTIVE INGREDIENTS: CAPSAICIN 0.25 mg/1 g
INACTIVE INGREDIENTS: CARBOXYMETHYLCELLULOSE SODIUM, UNSPECIFIED FORM; CASTOR OIL; DIHYDROXYALUMINUM AMINOACETATE; EDETATE DISODIUM; GLYCERIN; METHYLPARABEN; POLYACRYLIC ACID (250000 MW); POLYSORBATE 80; POLYVINYL ALCOHOL, UNSPECIFIED; PROPYLENE GLYCOL CAPRYLATE; WATER; SODIUM POLYACRYLATE (8000 MW); SORBITOL; TALC; TARTARIC ACID

Drug Facts - Equate Capsaicin Pain Relieving

Active ingredient

Capsaicin 0.025%

Purpose

Capsaicin - Topical analgesic

Uses

temporarily relieves minor aches and pains of muscles and joints due to

- simple backache
- arthritis
- strains
- sprains

Warnings

For external use only

When using this product

- use only as directed
- do not use at least 1 hours before, or immediately after, a bath or shower
- avoid contact with eyes and mucous membranes
- do not apply to wounds or to damaged or very sensitive skin
- do not bandage tightly or use with a heating pad

Stop use and ask a doctor if

- condition worsens
- excessive redness, irritation, burning or discomfort of the skin develops
- symptoms persist for more than 7 days or clear up and occur again within a few days

Keep out of reach of children.

If swallowed, get medical help or contact a Poison Control Center right away.

Directions

- adults and children 12 years and over: apply to affected area; change patch 1 to 2 times daily
- children under 12 years: ask a doctor
- FOR BEST RESULTS: apply to clean, dry skin
- tear open pouch and remove patch; if desired, cut patch to size
- grasp both ends of the patch firmly with thumbs near center
- stretch patch until the backing separates
- remove protective film while applying patch directly to site of pain
- WASH HANDS WITH SOAP AND WATER AFTER APPLYING

Inactive ingredients

carboxymethylcellulose sodium, castor oil, dihydroxyaluminum aminoacetate, edetate disodium, glycerin, methylparaben, partially neutralized polyacrylate, polyacrylic acid, polysorbate 80, polyvinyl alcohol, propylene glycol monocaprylate, purified water, sodium polyacrylate, sodium polyacrylate starch, sorbitol solution, talc, tartaric acid

Questions or comments?

Call 1-888-287-1915